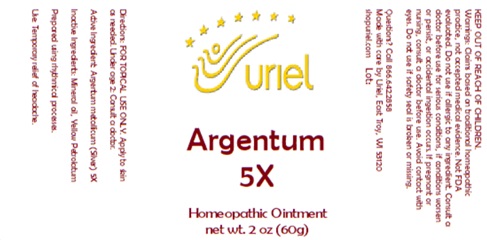 DRUG LABEL: Argentum 5X
NDC: 48951-1409 | Form: OINTMENT
Manufacturer: Uriel Pharmacy, Inc
Category: homeopathic | Type: HUMAN OTC DRUG LABEL
Date: 20260227

ACTIVE INGREDIENTS: COLLOIDAL SILVER 5 [hp_X]/1 g
INACTIVE INGREDIENTS: MINERAL OIL; PETROLATUM

Argentum 5X

INDICATIONS AND USAGE

Directions: FOR TOPICAL USE ONLY.

DOSAGE AND ADMINISTRATION

Apply to skin as needed. Under age 2: Consult a doctor.

Active Ingredient: Argentum metallicum (Silver) 5X

Inactive Ingredients: Mineral oil, Yellow Petrolatum

Prepared using rhythmical processes.

PURPOSE

Use: Temporary relief of headache.

KEEP OUT OF REACH OF CHILDREN.

WARNINGS

Warnings: Claims based on traditional homeopathic practice, not accepted medical evidence. Not FDA evaluated. Do not use if allergic to any ingredient. Consult a doctor before use for serious conditions, if conditions worsen or persist, or accidental ingestion occurs. If pregnant or nursing, consult a doctor before use. Avoid contact with eyes. Do not use if safety seal is broken or missing.

Questions? Call 866.642.2858
Made with care by Uriel, East Troy, WI 53120
shopuriel.com Lot: